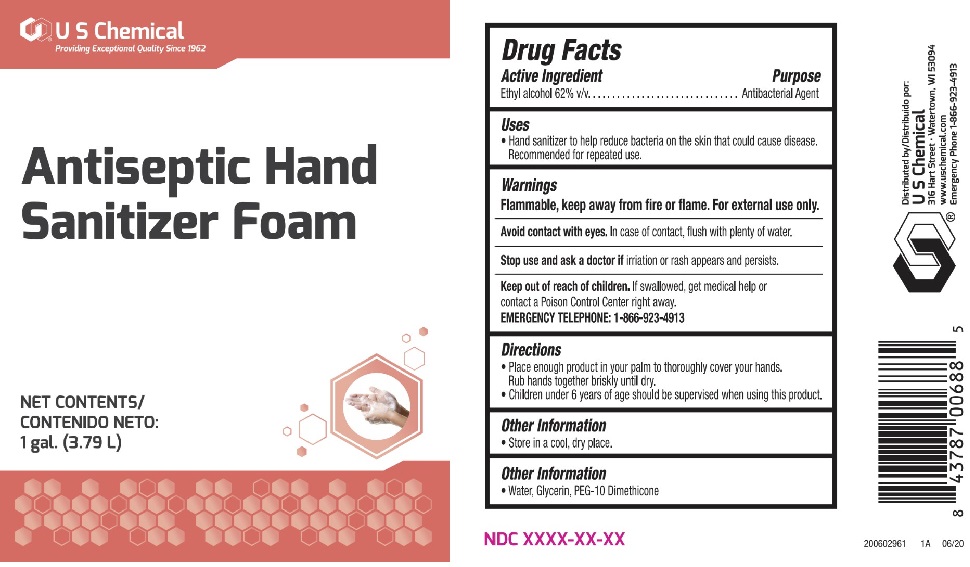 DRUG LABEL: Antiseptic Hand Sanitizer Foam
NDC: 61307-105 | Form: LIQUID
Manufacturer: US Chemical Corporation
Category: otc | Type: HUMAN OTC DRUG LABEL
Date: 20200615

ACTIVE INGREDIENTS: ALCOHOL 0.62 mL/1 mL
INACTIVE INGREDIENTS: WATER; GLYCERIN; PEG-10 DIMETHICONE (600 CST)

U S Chemical Antiseptic Hand Sanitizer Foam

Active Ingredient

Ethyl alcohol 62% v/v

Purpose

Antibacterial Agent

Uses

• Hand sanitizer to help reduce bacteria on the skin that could cause disease. Recommended for repeated use.

Warnings

Flammable, keep away from fire or flame. For external use only.

Avoid contact with eyes. In case of contact, flush with plenty of water.

Stop use and ask a doctor if irritation or rash appears and persists.

Keep out of reach of children. If swallowed, get medical help or contact a Poison Control Center right away.

EMERGENCY TELEPHONE: 1-866-923-4913

Directions

• Place enough product in your palm to thoroughly cover your hands. Rub hands together briskly until dry.

• Children under 6 years of age should be supervised when using this product.

Other Information

• Store in a cool, dry place.

Inactive Ingredient

• Water, Glycerin, PEG-10 Dimethicone

Providing Exceptional Quality Since 1962

Distributed by/Distribuido por:

U S Chemical

316 Hart Street · Watertown, WI 53094

www.uschemical.com

Emergency Phone 1-866-923-4913